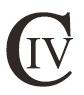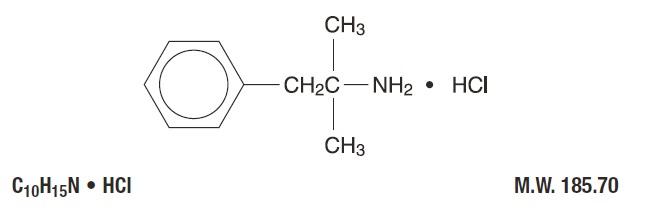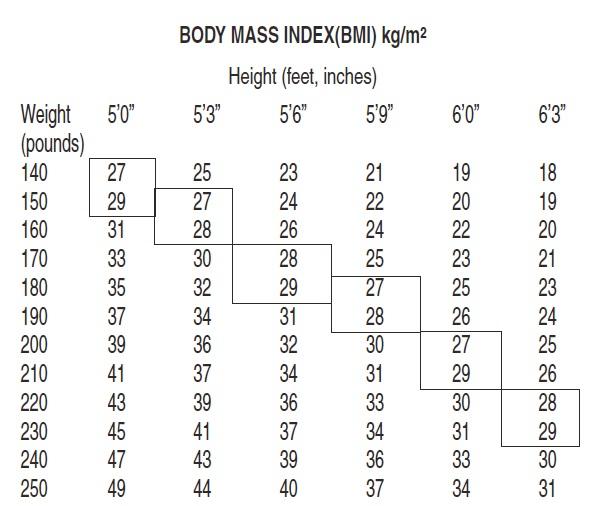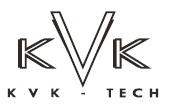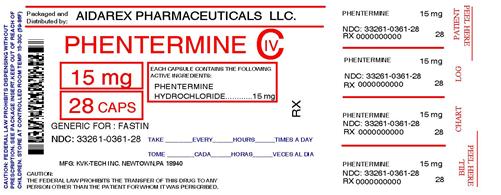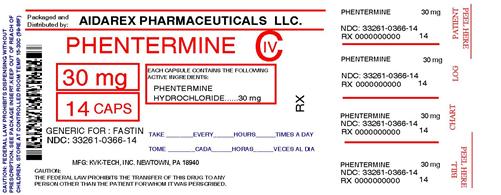 DRUG LABEL: Phentermine Hydrochloride
NDC: 33261-361 | Form: CAPSULE
Manufacturer: Aidarex Pharmaceuticals LLC
Category: prescription | Type: HUMAN PRESCRIPTION DRUG LABEL
Date: 20121004
DEA Schedule: CIV

ACTIVE INGREDIENTS: PHENTERMINE HYDROCHLORIDE 15 mg/1 1
INACTIVE INGREDIENTS: STARCH, CORN; GELATIN; LACTOSE MONOHYDRATE; D&C YELLOW NO. 10; FD&C BLUE NO. 1; FD&C RED NO. 3; FD&C RED NO. 40; TITANIUM DIOXIDE; MAGNESIUM STEARATE

Unknown Title

Phentermine Hydrochloride Capsules, USP

Rx Only

DESCRIPTION

Phentermine hydrochloride has the chemical name of α, α, -Dimethylphenethylamine hydrochloride. The structural formula is as follows:

Phentermine hydrochloride, is a white, odorless, hygroscopic, crystalline powder which is soluble in water and lower alcohols; slightly soluble in chloroform and insoluble in ether.

Phentermine hydrochloride, an anorectic agent for oral administration, is available as:

a) powder-filled capsules containing 15 mg Phentermine hydrochloride (equivalent to 12 mg Phentermine) or 30 mg Phentermine hydrochloride (equivalent to 24 mg Phentermine) and inactive ingredients: corn starch, gelatin, lactose monohydrate and magnesium stearate. In addition, the 15 mg capsules contain D&C Yellow #10, FD&C Blue #1, FD&C Red #3, FD&C Red #40, titanium dioxide and the 30 mg capsules contain D&C Yellow #10, FD&C Red #3, titanium dioxide.

b) bead-filled capsules containing 30 mg Phentermine hydrochloride (equivalent to 24 mg Phentermine) and inactive ingredients: corn starch, sucrose, hypromellose, povidone, and talc. In addition, the capsule contains FD&C blue #1/Brilliant blue FCF aluminum lake, D&C red #28 and gelatin.

CLINICAL PHARMACOLOGY

Phentermine is a sympathomimetic amine with pharmacologic activity similar to the prototype drugs of this class used in obesity, the amphetamines. Actions include central nervous system stimulation and elevation of blood pressure. Tachyphylaxis and tolerance have been demonstrated with all drugs of this class in which these phenomena have been looked for.

Drugs of this class used in obesity are commonly known as “anorectics” or “anorexigenics.” It has not been established that the action of such drugs in treating obesity is primarily one of appetite suppression. Other central nervous system actions, or metabolic effects, may be involved, for example. Adult obese subjects instructed in dietary management and treated with “anorectic” drugs lose more weight on the average than those treated with placebo and diet, as determined in relatively short-term clinical trials. The magnitude of increased weight loss of drug-treated patients over placebo-treated patients is only a fraction of a pound a week. The rate of weight loss is greatest in the first weeks of therapy for both drug and placebo subjects and tends to decrease in succeeding weeks. The possible origins of the increased weight loss due to the various drug effects are not established. The amount of weight loss associated with the use of an “anorectic” drug varies from trial to trial, and the increased weight loss appears to be related in part to variables other than the drugs prescribed, such as the physician-investigator, the population treated and the diet prescribed. Studies do not permit conclusions as to the relative importance of the drug and non-drug factors on weight loss.

The natural history of obesity is measured in years, whereas the studies cited are restricted to a few weeks’ duration; thus, the total impact of drug induced weight loss over that of diet alone must be considered clinically limited.

INDICATIONS AND USAGE

Phentermine hydrochloride is indicated as a short-term (a few weeks) adjunct in a regimen of weight reduction based on exercise, behavioral modification and caloric restriction in the management of exogenous obesity for patients with an initial body mass index ≥30 kg/m2, or ≥27 kg/m2 in the presence of other risk factors (e.g., hypertension, diabetes, hyperlipidemia).

Below is a chart of Body Mass Index (BMI) based on various heights and weights.

BMI is calculated by taking the patient’s weight, in kilograms (kg), divided by the patient’s height, in meters (m), squared. Metric conversions are as follows: pounds ÷ 2.2 = kg; inches x 0.0254 = meters.

The limited usefulness of agents of this class (see CLINICAL PHARMACOLOGY) should be measured against possible risk factors inherent in their use such as those described below.

CONTRAINDICATIONS

Advanced arteriosclerosis, cardiovascular disease, moderate to severe hypertension, hyperthyroidism, known hypersensitivity or idiosyncrasy to the sympathomimetic amines, glaucoma.

Agitated states.

Patients with history of drug abuse.

During or within 14 days following the administration of monoamine oxidase inhibitors (hypertensive crises may result).

WARNINGS

Phentermine hydrochloride capsules are indicated only as short-term monotherapy for the management of exogenous obesity. The safety and efficacy of combination therapy with phentermine and any other drug products for weight loss, including selective serotonin reuptake inhibitors (e.g., fluoxetine, sertraline, fluvoxamine, paroxetine), have not been established. Therefore, coadministration of these drug products for weight loss is not recommended.

Primary Pulmonary Hypertension (PPH) – a rare, frequently fatal disease of the lungs – has been reported to occur in patients receiving a combination of phentermine with fenfluramine or dexfenfluramine. The possibility of an association between PPH and the use of phentermine alone cannot be ruled out; there have been rare cases of PPH in patients who reportedly have taken phentermine alone. The initial symptom of PPH is usually dyspnea. Other initial symptoms include: angina pectoris, syncope or lower extremity edema. Patients should be advised to report immediately any deterioration in exercise tolerance. Treatment should be discontinued in patients who develop new, unexplained symptoms of dyspnea, angina pectoris, syncope or lower extremity edema.

Valvular Heart Disease: Serious regurgitant cardiac valvular disease, primarily affecting the mitral, aortic and/or tricuspid valves, has been reported in otherwise healthy persons who had taken a combination of phentermine with fenfluramine or dexfenfluramine for weight loss. The etiology of these valvulopathies has not been established and their course in individuals after the drugs are stopped is not known. The possibility of an association between valvular heart disease and

the use of phentermine alone cannot be ruled out; there have been rare cases of valvular heart disease in patients who reportedly have taken phentermine alone.

Tolerance to the anorectic effect usually develops within a few weeks. When this occurs, the recommended dose should not be exceeded in an attempt to increase the effect; rather, the drug should be discontinued. Phentermine may impair the ability of the patient to engage in potentially hazardous activities such as operating machinery or driving a motor vehicle; the patient should therefore be cautioned accordingly.

Usage with Alcohol: Concomitant use of alcohol with phentermine may result in an adverse drug interaction.

PRECAUTIONS

General

Caution is to be exercised in prescribing phentermine hydrochloride for patients with even mild hypertension. Insulin requirements in diabetes mellitus may be altered in association with the use of phentermine and the concomitant dietary regimen.

Phentermine may decrease the hypotensive effect of guanethidine. The least amount feasible should be prescribed or dispensed at one time in order to minimize the possibility of overdosage.

Carcinogenesis, Mutagenesis, Impairment of Fertility: Studies have not been performed with phentermine hydrochloride to determine the potential for carcinogenesis, mutagenesis or impairment of fertility.

Pregnancy-Teratogenic Effects: Pregnancy Category C. Animal reproduction studies have not been conducted with phentermine hydrochloride. It is also not known whether phentermine hydrochloride can cause fetal harm when administered to a pregnant woman or can affect reproductive capacity. Phentermine should be given to a pregnant woman only if clearly needed.

Nursing Mothers

Because of the potential for serious adverse reactions in nursing infants, a decision should be made whether to discontinue nursing or to discontinue the drug, taking into account the importance of the drug to the mother.

Pediatric Use

Safety and effectiveness in pediatric patients have not been established.

ADVERSE REACTIONS

Cardiovascular: Primary pulmonary hypertension and/or regurgitant cardiac valvular disease (see WARNINGS), palpitation, tachycardia, elevation of blood pressure.

Central Nervous System: Overstimulation, restlessness, dizziness, insomnia, euphoria, dysphoria, tremor, headache; rarely psychotic episodes at recommended doses.

Gastrointestinal: Dryness of the mouth, unpleasant taste, diarrhea, constipation, other gastrointestinal disturbances.

Allergic: Urticaria.

Endocrine: Impotence, changes in libido.

DRUG ABUSE AND DEPENDENCE

Phentermine is related chemically and pharmacologically to the amphetamines. Amphetamines and related stimulant drugs have been extensively abused, and the possibility of abuse of phentermine should be kept in mind when evaluating the desirability of including a drug as part of a weight reduction program. Abuse of amphetamines and related drugs may be associated with intense psychological dependence and severe social dysfunction. There are reports of patients who have increased the dosage to many times that recommended. Abrupt cessation following prolonged high dosage administration results in extreme fatigue and mental depression; changes are also noted on the sleep EEG. Manifestations of chronic intoxication with anorectic drugs include severe dermatoses, marked insomnia, irritability, hyperactivity and personality changes. The most severe manifestation of chronic intoxications is psychosis, often clinically indistinguishable from schizophrenia.

OVERDOSAGE

Manifestations of acute overdosage with phentermine include restlessness, tremor, hyperreflexia, rapid respiration, confusion, assaultiveness, hallucinations, panic states. Fatigue and depression usually follow the central stimulation. Cardiovascular effects include arrhythmias, hypertension or hypotension, and circulatory collapse. Gastrointestinal symptoms include nausea, vomiting, diarrhea and abdominal cramps. Fatal poisoning usually terminates in convulsions and coma.

Management of acute phentermine intoxication is largely symptomatic and includes lavage and sedation with a barbiturate. Experience with hemodialysis or peritoneal dialysis is inadequate to permit recommendations in this regard. Acidification of the urine increases phentermine excretion. Intravenous phentolamine has been suggested for possible acute, severe hypertension, if this complicates phentermine overdosage.

DOSAGE AND ADMINISTRATION

Dosage should be individualized to obtain an adequate response with the lowest effective dose.

Exogenous Obesity: The usual adult dose is 15 mg to 30 mg at approximately 2 hours after breakfast for appetite control. Late evening medication should be avoided because of the possibility of resulting insomnia. Administration of one capsule (30 mg) daily has been found to be adequate in depression of the appetite for 12 to 14 hours.

Phentermine is not recommended for use in patients 16 years of age and under.

HOW SUPPLIED

Phentermine hydrochloride capsules, USP are available as follows:

Phentermine hydrochloride capsules, USP 15 mg are supplied as gray opaque cap, rich yellow opaque body with black imprint “K 26” on both the cap and body, filled with powder.

Bottles of 7, NDC 33261-361-07
Bottles of 8, NDC 33261-361-08
Bottles of 14, NDC 33261-361-14
Bottles of 15, NDC 33261-361-15
Bottles of 23, NDC 33261-361-23
Bottles of 28, NDC 33261-361-28
Bottles of 30, NDC 33261-361-30
Bottles of 40, NDC 33261-361-40
Bottles of 45, NDC 33261-361-45
Bottles of 60, NDC 33261-361-60

Phentermine hydrochloride capsules, USP 30 mg are supplied as blue cap, natural body with black imprint “K 28” on both the cap and body, filled with white and blue colored beads.

Bottles of 7, NDC 33261-366-07
Bottles of 8, NDC 33261-366-08
Bottles of 14, NDC 33261-366-14
Bottles of 15, NDC 33261-366-15
Bottles of 23, NDC 33261-366-23
Bottles of 28, NDC 33261-366-28
Bottles of 30, NDC 33261-366-30
Bottles of 40, NDC 33261-366-40
Bottles of 45, NDC 33261-366-45
Bottles of 60, NDC 33261-366-60

Store at 20° to 25°C (68° to 77°F) with excursions permitted between 15° to 30°C (59° to 86°F) [See USP Controlled Room Temperature]. Protect from moisture.

Dispense in a tight, light resistant container as defined in the USP, with a child-resistant closure (as required). Protect from moisture.

Manufactured by:

KVK-TECH INC.

110 Terry Drive

Newtown, PA 18940.

Item ID # 006070/00

Manufacturer’s Code: 10702 03/08

Repackaged By:
Aidarex Pharmaceuticals, LLC
Corona, CA 92280